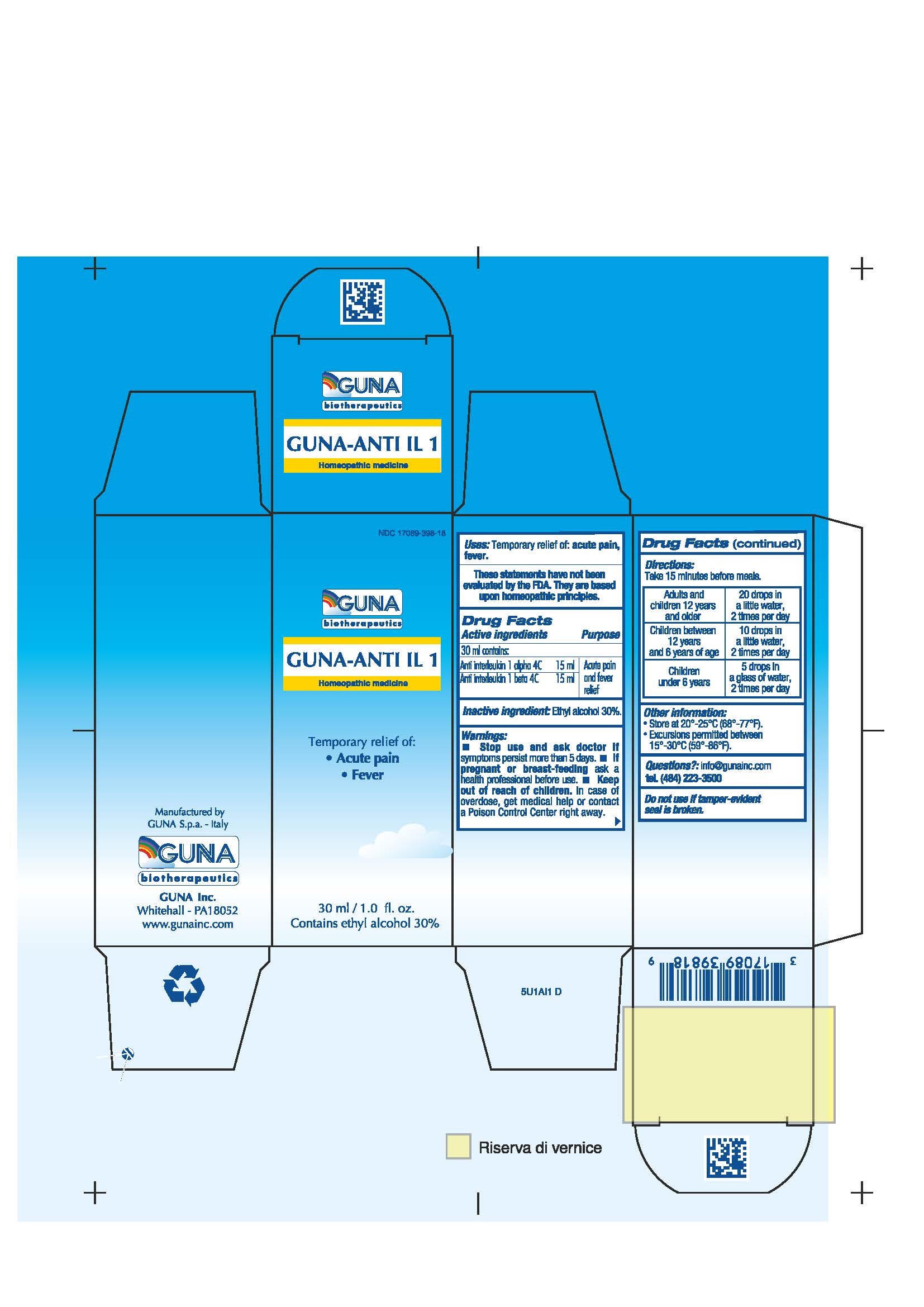 DRUG LABEL: GUNA-ANTI IL 1
NDC: 17089-398 | Form: SOLUTION/ DROPS
Manufacturer: Guna spa
Category: homeopathic | Type: HUMAN OTC DRUG LABEL
Date: 20221115

ACTIVE INGREDIENTS: ANTI-INTERLEUKIN-1.ALPHA. IMMUNOGLOBULIN G RABBIT 4 [hp_C]/30 mL; CANAKINUMAB 4 [hp_C]/30 mL
INACTIVE INGREDIENTS: ALCOHOL 9 mL/30 mL

GUNA-ANTI IL1

ACTIVE INGREDIENTS/PURPOSE

ANTI INTERLEUKIN 1 ALPHA 4C ACUTE PAIN AND FEVER RELIEF
ANTI INTERLEUKIN 1 BETA 4C ACUTE PAIN AND FEVER RELIEF

USES

Temporary relief of:

- Acute pain
- Fever

WARNINGS

- Stop use and ask doctor if symptoms persist more than 5 days.
- If pregnant or breast-feeding ask a health professional before use.
- Keep out of reach of children. In case of overdose, get medical help or contact a Poison Control Center right away.
- Contains ethyl alcohol 30%

PREGNANCY

If pregnant or breast-feeding ask a doctor before use.

WARNINGS

Keepout of reach of children.

DIRECTIONS

Adults and children 12 years and older 20 drops twice a day in a little water. Hold in the mouth for about 30 seconds then swallow.
Children between 12 years and 6 years of age 10 drops twice a day in a little water. Hold in the mouth for about 30 seconds then swallow.
Children under 6 years 5 drops twice a day in a glass of water.

QUESTIONS

Questions?: info@gunainc.com
Tel. (484) 223-3500

INDICATIONS AND USAGE

Take 15 minutes before meals.

Inactive ingredient: Ethyl alcohol 30%.